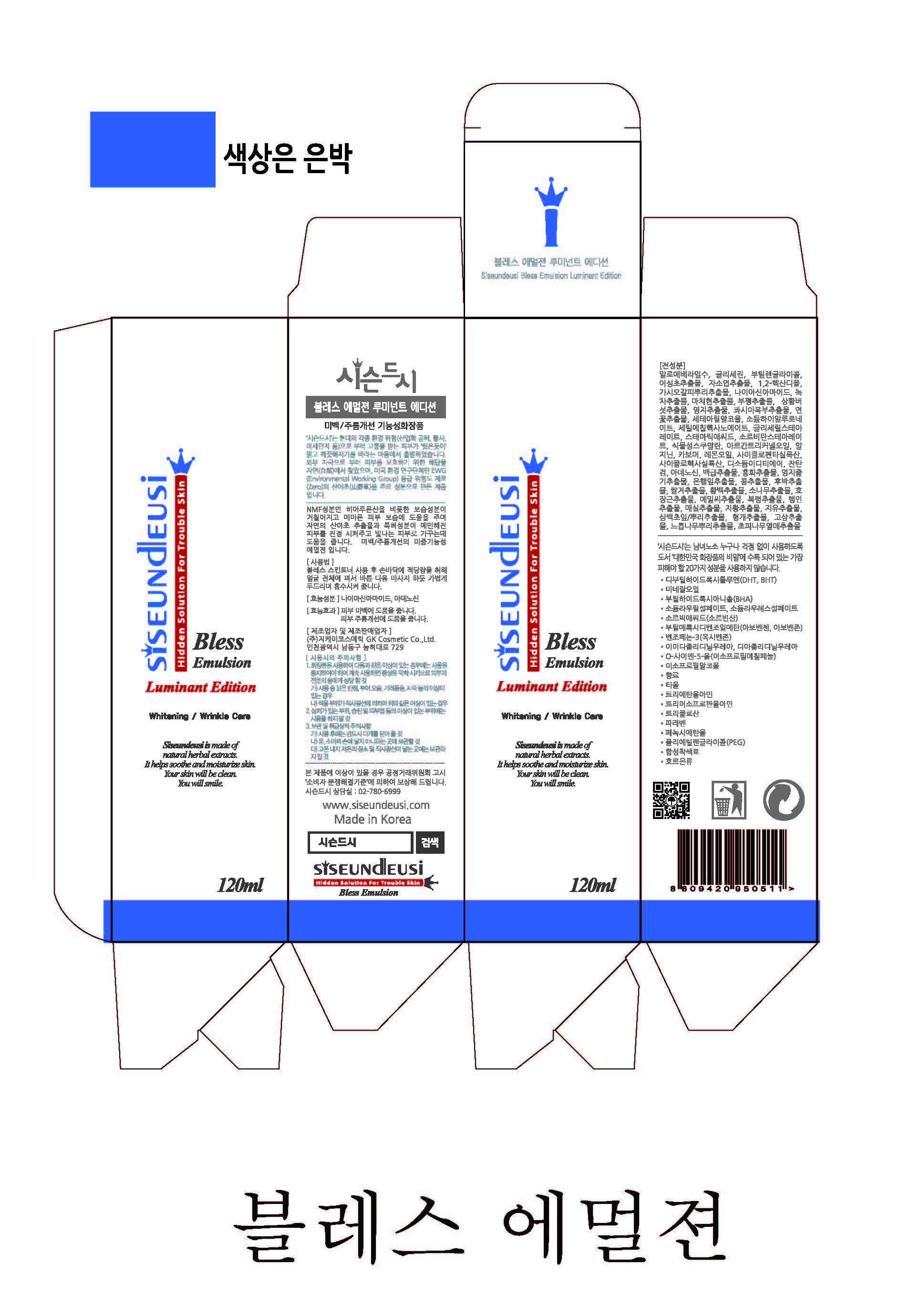 DRUG LABEL: SISEUNDEUSI LUMINANT
NDC: 70098-0006 | Form: EMULSION
Manufacturer: GK COSMETIC CO., LTD.
Category: otc | Type: HUMAN OTC DRUG LABEL
Date: 20170206

ACTIVE INGREDIENTS: NIACINAMIDE 2 g/100 mL; ADENOSINE 0.04 g/100 mL
INACTIVE INGREDIENTS: BUTYLENE GLYCOL; GLYCERIN; ALOE VERA LEAF

Drug Facts

ACTIVE INGREDIENT

Niacinamide, Adenosine

INACTIVE INGREDIENT

Aloe Barbadensis Leaf Water, Glycerin, Butylene Glycol, Houttuynia Cordata Extract, Perilla Frutescens Leaf Extract, 1,2-Hexanediol, Acanthopanax Senticosus (Eleuthero) Root Extract, Camellia Sinensis Leaf Extract, Portulaca Oleracea Extract, Spirodela Polyrrhiza Extract, Phellinus Linteus Extract, Ganoderma Lucidum (Mushroom) Extract, Picrasma Excelsa Wood Extract, Nelumbium Speciosum Flower Extract, Cetearyl Alcohol, Sodium Hyaluronate, Cetyl Ethylhexanoate, Glyceryl Stearate, Stearic Acid, Sorbitan Stearate, Phytosqualane, Argania Spinosa Kernel Oil, Arginine , Carbomer, Citrus Limon (Lemon) Fruit Oil, Cyclopentasiloxane, Cyclohexasiloxane, Disodium EDTA, Xanthan Gum, Bletilla Striata Root Extract, Carthamus Tinctorius (Safflower) Flower Extract, Ganoderma Lucidum (Mushroom) Stem Extract, Ginkgo Biloba Leaf Extract, Glycine Soja (Soybean) Seed Extract, Magnolia Obovata Bark Extract, Oryza Sativa (Rice) Bran Extract, Phellodendron Amurense Bark Extract, Pinus Densiflora Extract, Polygonum Cuspidatum Root Extract, Polygonum Fagopyrum Seed Extract, Poria Cocos Extract, Prunus Armeniaca (Apricot) Kernel Extract, Prunus Mume Fruit Extract, Rehmannia Glutinosa Root Extract, Sanguisorba Officinalis Root Extract, Saururus Chinensis Leaf/Root Extract, Schizonepeta Tenuifolia Extract, Sophora Angustifolia Root Extract, Ulmus Davidiana Root Extract, Zanthoxylum Piperitum Fruit Extract

PURPOSE

Whitening, Anti-Wrinkle

keep out of reach of the children

INDICATIONS AND USAGE

After using bless luminant skin toner, put appropriate amount of emulsion on your face and gently dap your face for a few moments to help your skin to absorb emulsion.

DOSAGE AND ADMINISTRATION

for external use only

WARNINGS

1. Do not use in the following cases(Eczema and scalp wounds)
2.Side Effects
1)Due to the use of this druf if rash, irritation, itching and symptopms of hypersnesitivity occur dicontinue use and consult your phamacisr or doctor
3.General Precautions
1)If in contact with the eyes, wash out thoroughty with water If the symptoms are servere, seek medical advice immediately
2)This product is for exeternal use only. Do not use for internal use
4.Storage and handling precautions
1)If possible, avoid direct sunlight and store in cool and area of low humidity
2)In order to maintain the quality of the product and avoid misuse
3)Avoid placing the product near fire and store out in reach of children